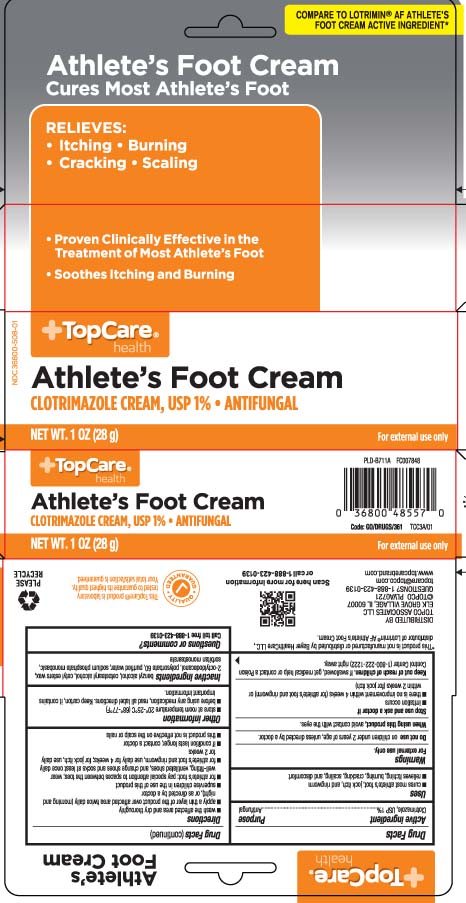 DRUG LABEL: Clotrimazole
NDC: 36800-508 | Form: CREAM
Manufacturer: TOP CARE (Topco Associates LLC)
Category: otc | Type: HUMAN OTC DRUG LABEL
Date: 20241113

ACTIVE INGREDIENTS: CLOTRIMAZOLE 10 mg/1 g
INACTIVE INGREDIENTS: BENZYL ALCOHOL; CETOSTEARYL ALCOHOL; CETYL ESTERS WAX; OCTYLDODECANOL; POLYSORBATE 60; WATER; SODIUM PHOSPHATE, MONOBASIC, MONOHYDRATE; SORBITAN MONOSTEARATE

Clotrimazole Vaginal Cream, USP

Active ingredients

Clotrimazole, USP 1%

)

Purpose

Antifungal

Uses

- treats most athlete's foot, jock itch, and ringworm
- relieves itching, burning, cracking, scaling, and discomfort

Warnings

For external use only

Do not use

on children under 2 years of age, unless directed by a doctor.

When using this product,

avoid contact with the eyes.

Stop use and ask a doctor if

- irritation occurs
- there is no improvement within 4 weeks (for athlete's foots and ringworm) or within 2 weeks (for jock itch)

Keep out of reach of children

If swallowed, get medical help or contact a Poison Control Center (1-800-222-1222) right away.

Directions

- wash the affected area and dry thoroughly
- apply a thin layer of the product over affected area twice daily (morning and night), or as directed by a doctor
- supervise children in the use of this product
- for athlete's foot: pay special attention to spaces between the toes; wear well-fitting, ventilated shoes, and change shoes and socks at least once daily
- for athlete's foot and ringworm, use daily for 4 weeks; for jock itch, use daily for 2 weeks
- if condition lasts longer, contact a doctor
- this product is not effective on the scalp or nails

Other information

- store at room temperature 20º-25ºC (68º-77ºF)
- before using any medication, read all label directions. Keep carton, it contains important information.

Inactive ingredients

benzyl alcohol, cetostearyl alcohol, cetyl esters wax, 2-octyldodecanol, polysorbate 60, purified water, sodium phosphate monobasic, sorbitan monostearate

Question or comments?

Call toll free 1-888-423-0139

Principal display panel

COMPARE TO LOTRIMIN® AF ATHLETE'S FPPT CREAM ACTIVE INGREDIENT*

Athlete's Foot Cream

Cure Most Athlete's Foot

RELIEVES:

- Itching
- Burning
- Cracking
- Scaling
- Proven Clinically Effective in the Treatment of Most Athlete's Foot
- Soothes Itching and Burning

NET WT. OZ (g)

*This product is not manufactured or distributed by Bayer HealthCare LLC., distributor of Lotrimin® AF Athlete's Foot Cream.

DISTRIBUTED BY

TOPCO ASSOCIATES LLC

ELK GROVE VILLAGE, IL 60007

www.topcarebrand.com

Package label

TOPCARE HEALTH Athlete's Foot Cream